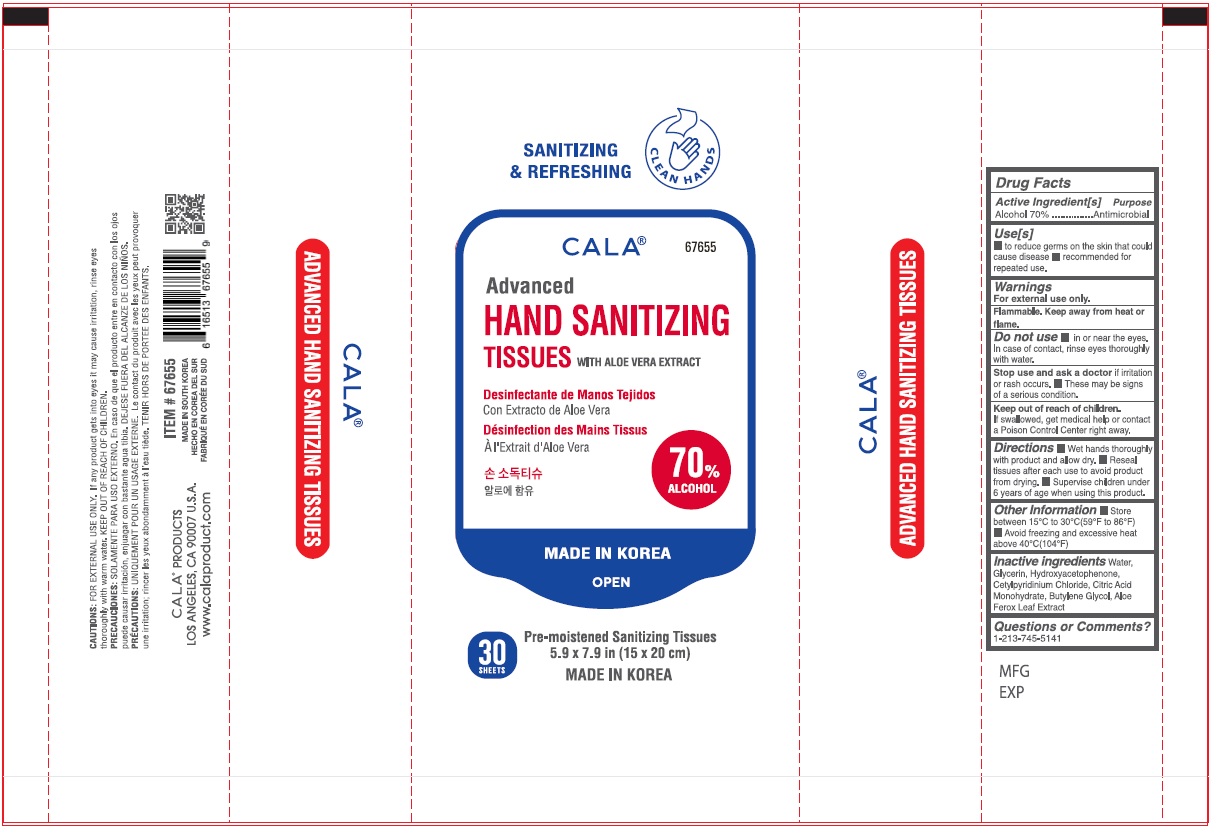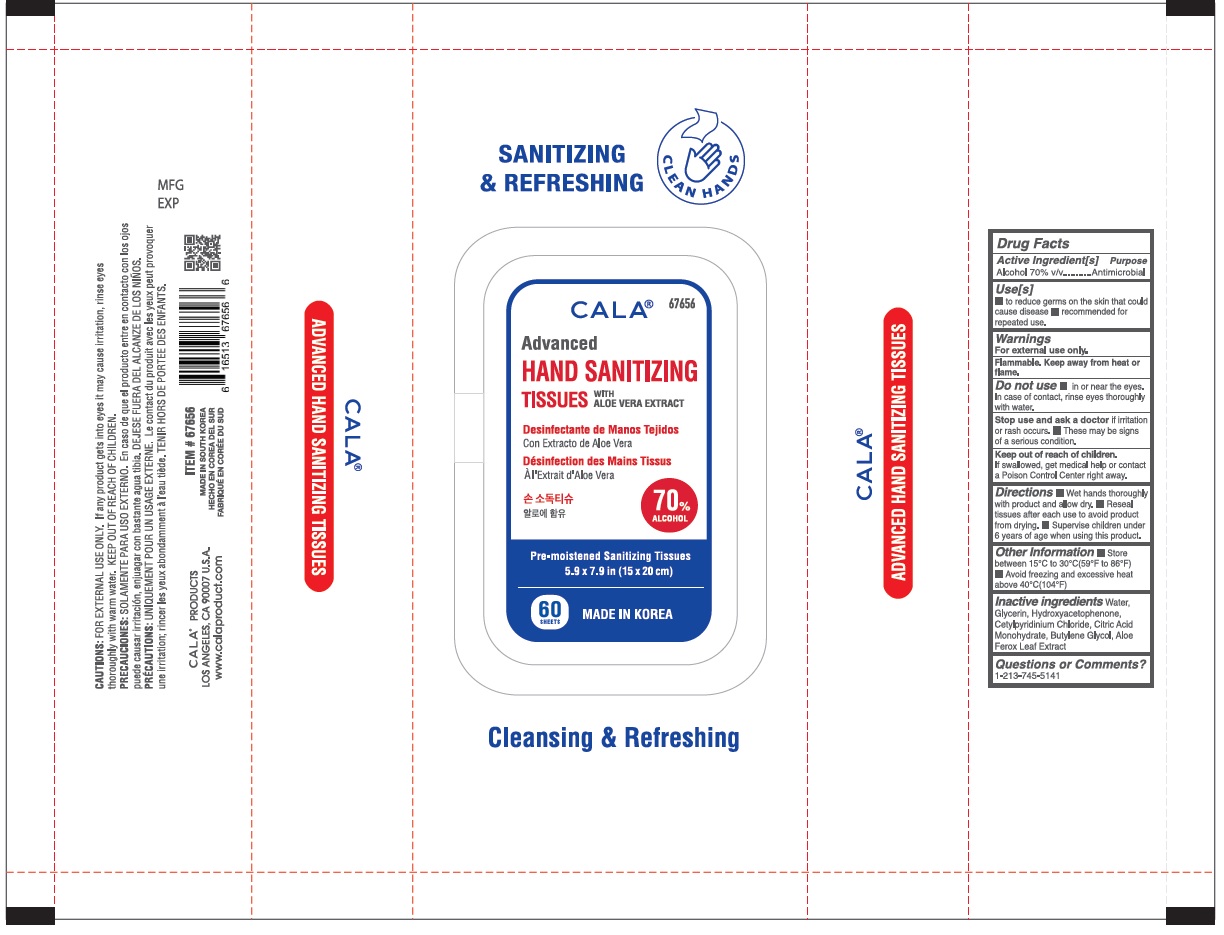 DRUG LABEL: CALA ADVANCED HAND SANITIZING TISSUES
NDC: 74985-678 | Form: SWAB
Manufacturer: Shin's Trading Co., Inc. Dba Cala Products
Category: otc | Type: HUMAN OTC DRUG LABEL
Date: 20200916

ACTIVE INGREDIENTS: ALCOHOL 70 mL/100 mL
INACTIVE INGREDIENTS: WATER; GLYCERIN; HYDROXYACETOPHENONE; CETYLPYRIDINIUM CHLORIDE; CITRIC ACID MONOHYDRATE; BUTYLENE GLYCOL; ALOE FEROX LEAF

CALA® Advanced HAND SANITIZING TISSUES

Active Ingredient[s]

Alcohol 70% v/v

Purpose

Antimicrobial

Use[s]

■ to reduce germs on the skin that could cause disease ■ recommended for repeated use.

Warnings

For external use only

Flammable. Keep away from heat or flame.

Do not use ■ in or near the eyes. In case of contact, rinse eyes thoroughly with water.

Stop use and ask a doctor if irritation or rash occurs. ■ These may be signs of a serious condition.

Keep out of reach of children.

If swallowed, get medical help or contact a Poison Control Center right away.

DOSAGE AND ADMINISTRATION

Directions ■ Wet hands thoroughly with product and allow dry. ■ Reseal tissues after each use to avoid product from drying. ■ Supervise children under 6 years of age when using this product.

Other Information ■ Store between 15°C to 30°C(59°F to 86°F) ■ Avoid freezing and excessive heat above 40°C(104°F)

INACTIVE INGREDIENT

Inactive ingredients Water, Glycerin, Hydroxyacetophenone, Cetylpyridinium Chloride, Citric Acid Monohydrate, Butylene Glycol, Aloe Ferox Leaf Extract

Questions or Comments?

1-231-745-5141

SANITIZING & REFRESHING

CLEAN HANDS

WITH ALOE VERA EXTRACT

Pre-moistened Santizing Tissues

5.9 x 7.9 in (15 x 20 cm)

MADE IN KOREA

Cleansing & Refreshing

ADVANCED HAND SANITIZING TISSUES

CAUTIONS: FOR EXTERNAL USE ONLY. If any product gets into eyes it may cause irritation, rinse eyes thoroughly with warm water. KEEP OUT OF REACH OF CHILDREN.

CALA® PRODUCTS

LOS ANGELES, CA 90007 U.S.A.

www.calaproduct.com

MADE IN SOUTH KOREA